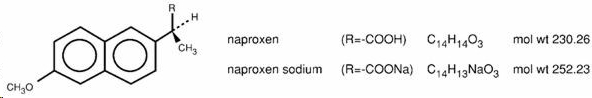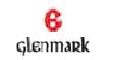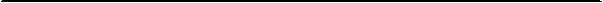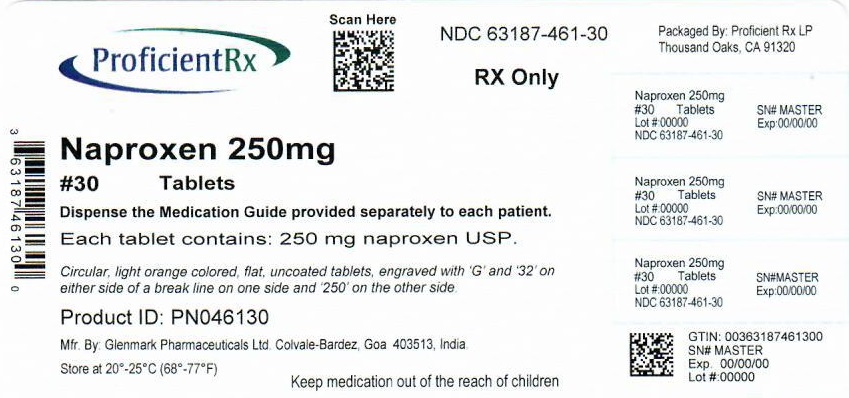 DRUG LABEL: Naproxen
NDC: 63187-461 | Form: TABLET
Manufacturer: Proficient Rx LP
Category: prescription | Type: HUMAN PRESCRIPTION DRUG LABEL
Date: 20220401

ACTIVE INGREDIENTS: NAPROXEN 250 mg/1 1
INACTIVE INGREDIENTS: MICROCRYSTALLINE CELLULOSE; CROSCARMELLOSE SODIUM; POVIDONE, UNSPECIFIED; MAGNESIUM STEARATE; FERRIC OXIDE RED; FERRIC OXIDE YELLOW

NAPROXEN Tablets, USP
NAPROXEN SODIUM Tablets, USP

Rx Only

BOXED WARNING

Cardiovascular Risk

• NSAIDs may cause an increased risk of serious cardiovascular thrombotic events, myocardial infarction, and stroke, which can be fatal. This risk may increase with duration of use. Patients with cardiovascular disease or risk factors for cardiovascular disease may be at greater risk (see WARNINGS).

• Naproxen as naproxen tablets or naproxen sodium tablets is contraindicated for the treatment of peri-operative pain in the setting of coronary artery bypass graft (CABG) surgery (see WARNINGS).

Gastrointestinal Risk

• NSAIDs cause an increased risk of serious gastrointestinal adverse events including bleeding, ulceration, and perforation of the stomach or intestines, which can be fatal. These events can occur at any time during use and without warning symptoms. Elderly patients are at greater risk for serious gastrointestinal events (see WARNINGS).

DESCRIPTION

Naproxen USP is a proprionic acid derivative related to the arylacetic acid group of nonsteroidal anti-inflammatory drugs.

The chemical names for naproxen USP and naproxen sodium USP are (S)-6-methoxy-α-methyl-2-naphthaleneacetic acid and (S)-6-methoxy-α-methyl-2-naphthaleneacetic acid, sodium salt, respectively. Naproxen USP and naproxen sodium USP have the following structures, respectively:

Naproxen USP has a molecular weight of 230.26 and a molecular formula of C14H14O3. Naproxen sodium USP has a molecular weight of 252.23 and a molecular formula of C14H13NaO3.

Naproxen USP is an odorless, white to off-white crystalline substance. It is lipid-soluble, practically insoluble in water at low pH and freely soluble in water at high pH. The octanol/water partition coefficient of naproxen USP at pH 7.4 is 1.6 to 1.8. Naproxen sodium USP is a white to creamy white, crystalline solid, freely soluble in water at neutral pH.

Naproxen tablets USP are available as light orange colored tablets containing 250 mg of naproxen USP, light orange colored tablets containing 375 mg of naproxen USP and light orange colored tablets containing 500 mg of naproxen USP for oral administration. The inactive ingredients are microcrystalline cellulose, croscarmellose sodium, iron oxides, povidone and magnesium stearate.

Naproxen sodium tablets USP are available as blue tablets containing 275 mg of naproxen sodium USP and as blue tablets containing 550 mg of naproxen sodium USP for oral administration. The inactive ingredients are croscarmellose sodium, colloidal silicon dioxide, povidone, magnesium stearate, microcrystalline cellulose and talc. The coating suspension for the naproxen sodium 275 mg tablet may contain Opadry blue 03F50544. The coating suspension for the naproxen sodium 550 mg tablet may contain Opadry blue 03F50544.

CLINICAL PHARMACOLOGY

Pharmacodynamics

Naproxen is a nonsteroidal anti-inflammatory drug (NSAID) with analgesic and antipyretic properties. The sodium salt of naproxen has been developed as a more rapidly absorbed formulation of naproxen for use as an analgesic. The mechanism of action of the naproxen anion, like that of other NSAIDs, is not completely understood but may be related to prostaglandin synthetase inhibition.

Pharmacokinetics

Naproxen and naproxen sodium are rapidly and completely absorbed from the gastrointestinal tract with an in vivo bioavailability of 95%. The different dosage forms of naproxen are bioequivalent in terms of extent of absorption (AUC) and peak concentration (Cmax); however, the products do differ in their pattern of absorption. These differences between naproxen products are related to both the chemical form of naproxen used and its formulation. Even with the observed differences in pattern of absorption, the elimination half-life of naproxen is unchanged across products ranging from 12 to 17 hours. Steady-state levels of naproxen are reached in 4 to 5 days, and the degree of naproxen accumulation is consistent with this half-life. This suggests that the differences in pattern of release play only a negligible role in the attainment of steady-state plasma levels.

Absorption

Immediate Release

After administration of naproxen tablets, peak plasma levels are attained in 2 to 4 hours. After oral administration of naproxen sodium, peak plasma levels are attained in 1 to 2 hours. The difference in rates between the two products is due to the increased aqueous solubility of the sodium salt of naproxen used in naproxen sodium.

Distribution

Naproxen has a volume of distribution of 0.16 L/kg. At therapeutic levels naproxen is greater than 99% albumin-bound. At doses of naproxen greater than 500 mg/day there is less than proportional increase in plasma levels due to an increase in clearance caused by saturation of plasma protein binding at higher doses (average trough Css 36.5, 49.2 and 56.4 mg/L with 500, 1000 and 1500 mg daily doses of naproxen, respectively). The naproxen anion has been found in the milk of lactating women at a concentration equivalent to approximately 1% of maximum naproxen concentration in plasma (see PRECAUTIONS, Nursing Mothers).

Metabolism

Naproxen is extensively metabolized in the liver to 6-0-desmethyl naproxen, and both parent and metabolites do not induce metabolizing enzymes. Both naproxen and 6-0-desmethyl naproxen are further metabolized to their respective acylglucuronide conjugated metabolites.

Excretion

The clearance of naproxen is 0.13 mL/min/kg. Approximately 95% of the naproxen from any dose is excreted in the urine, primarily as naproxen (<1%), 6-0-desmethyl naproxen (<1%) or their conjugates (66% to 92%). The plasma half-life of the naproxen anion in humans ranges from 12 to 17 hours. The corresponding half-lives of both naproxen’s metabolites and conjugates are shorter than 12 hours, and their rates of excretion have been found to coincide closely with the rate of naproxen disappearance from the plasma. Small amounts, 3% or less of the administered dose, are excreted in the feces. In patients with renal failure metabolites may accumulate (see WARNINGS: Renal Effects).

Special Populations

Pediatric Patients

In pediatric patients aged 5 to 16 years with arthritis, plasma naproxen levels following a 5 mg/kg single dose of naproxen suspension (see DOSAGE AND ADMINISTRATION) were found to be similar to those found in normal adults following a 500 mg dose. The terminal half-life appears to be similar in pediatric and adult patients. Pharmacokinetic studies of naproxen were not performed in pediatric patients younger than 5 years of age. Pharmacokinetic parameters appear to be similar following administration of naproxen suspension or tablets in pediatric patients.

Geriatric Patients

Studies indicate that although total plasma concentration of naproxen is unchanged, the unbound plasma fraction of naproxen is increased in the elderly, although the unbound fraction is <1% of the total naproxen concentration. Unbound trough naproxen concentrations in elderly subjects have been reported to range from 0.12% to 0.19% of total naproxen concentration, compared with 0.05% to 0.075% in younger subjects. The clinical significance of this finding is unclear, although it is possible that the increase in free naproxen concentration could be associated with an increase in the rate of adverse events per a given dosage in some elderly patients.

Race

Pharmacokinetic differences due to race have not been studied.

Hepatic Insufficiency

Naproxen pharmacokinetics has not been determined in subjects with hepatic insufficiency.

Renal Insufficiency

Naproxen pharmacokinetics has not been determined in subjects with renal insufficiency. Given that naproxen, its metabolites and conjugates are primarily excreted by the kidney, the potential exists for naproxen metabolites to accumulate in the presence of renal insufficiency. Elimination of naproxen is decreased in patients with severe renal impairment. Naproxen-containing products are not recommended for use in patients with moderate to severe and severe renal impairment (creatinine clearance <30 mL/min) (see WARNINGS: Renal Effects).

CLINICAL STUDIES

General Information

Naproxen has been studied in patients with rheumatoid arthritis, osteoarthritis, juvenile arthritis, ankylosing spondylitis, tendonitis and bursitis, and acute gout. Improvement in patients treated for rheumatoid arthritis was demonstrated by a reduction in joint swelling, a reduction in duration of morning stiffness, a reduction in disease activity as assessed by both the investigator and patient, and by increased mobility as demonstrated by a reduction in walking time. Generally, response to naproxen has not been found to be dependent on age, sex, severity or duration of rheumatoid arthritis.

In patients with osteoarthritis, the therapeutic action of naproxen has been shown by a reduction in joint pain or tenderness, an increase in range of motion in knee joints, increased mobility as demonstrated by a reduction in walking time, and improvement in capacity to perform activities of daily living impaired by the disease.

In a clinical trial comparing standard formulations of naproxen 375 mg bid (750 mg a day) vs 750 mg bid (1500 mg/day), 9 patients in the 750 mg group terminated prematurely because of adverse events. Nineteen patients in the 1500 mg group terminated prematurely because of adverse events. Most of these adverse events were gastrointestinal events.

In clinical studies in patients with rheumatoid arthritis, osteoarthritis, and juvenile arthritis, naproxen has been shown to be comparable to aspirin and indomethacin in controlling the aforementioned measures of disease activity, but the frequency and severity of the milder gastrointestinal adverse effects (nausea, dyspepsia, heartburn) and nervous system adverse effects (tinnitus, dizziness, lightheadedness) were less in naproxen-treated patients than in those treated with aspirin or indomethacin.

In patients with ankylosing spondylitis, naproxen has been shown to decrease night pain, morning stiffness and pain at rest. In double-blind studies the drug was shown to be as effective as aspirin, but with fewer side effects.

In patients with acute gout, a favorable response to naproxen was shown by significant clearing of inflammatory changes (eg, decrease in swelling, heat) within 24 to 48 hours, as well as by relief of pain and tenderness.

Naproxen has been studied in patients with mild to moderate pain secondary to postoperative, orthopedic, postpartum episiotomy and uterine contraction pain and dysmenorrhea. Onset of pain relief can begin within 1 hour in patients taking naproxen and within 30 minutes in patients taking naproxen sodium. Analgesic effect was shown by such measures as reduction of pain intensity scores, increase in pain relief scores, decrease in numbers of patients requiring additional analgesic medication, and delay in time to remedication. The analgesic effect has been found to last for up to 12 hours.

Naproxen may be used safely in combination with gold salts and/or corticosteroids; however, in controlled clinical trials, when added to the regimen of patients receiving corticosteroids, it did not appear to cause greater improvement over that seen with corticosteroids alone. Whether naproxen has a “steroid-sparing” effect has not been adequately studied. When added to the regimen of patients receiving gold salts, naproxen did result in greater improvement. Its use in combination with salicylates is not recommended because there is evidence that aspirin increases the rate of excretion of naproxen and data are inadequate to demonstrate that naproxen and aspirin produce greater improvement over that achieved with aspirin alone. In addition, as with other NSAIDs, the combination may result in higher frequency of adverse events than demonstrated for either product alone.

In ^51Cr blood loss and gastroscopy studies with normal volunteers, daily administration of 1000 mg of naproxen as 1000 mg of naproxen tablets or 1100 mg of naproxen sodium tablets has been demonstrated to cause statistically significantly less gastric bleeding and erosion than 3250 mg of aspirin.

Three 6-week, double-blind, multicenter studies with naproxen delayed release (375 or 500 mg bid, n=385) and naproxen (375 or 500 mg bid, n=279) were conducted comparing naproxen delayed release with naproxen including 355 rheumatoid arthritis and osteoarthritis patients who had a recent history of NSAID-related GI symptoms. These studies indicated that naproxen delayed release and naproxen showed no significant differences in efficacy or safety and had similar prevalence of minor GI complaints. Individual patients, however, may find one formulation preferable to the other.

Geriatric Patients

The hepatic and renal tolerability of long-term naproxen administration was studied in two double-blind clinical trials involving 586 patients. Of the patients studied, 98 patients were age 65 and older and 10 of the 98 patients were age 75 and older. Naproxen was administered at doses of 375 mg twice daily or 750 mg twice daily for up to 6 months. Transient abnormalities of laboratory tests assessing hepatic and renal function were noted in some patients, although there were no differences noted in the occurrence of abnormal values among different age groups.

INDICATIONS AND USAGE

Carefully consider the potential benefits and risks of naproxen, naproxen sodium and other treatment options before deciding to use naproxen or naproxen sodium tablets. Use the lowest effective dose for the shortest duration consistent with individual patient treatment goals (see WARNINGS).

Naproxen as naproxen tablets or naproxen sodium tablets are indicated:

- For the relief of the signs and symptoms of rheumatoid arthritis
- For the relief of the signs and symptoms of osteoarthritis
- For the relief of the signs and symptoms of ankylosing spondylitis
- For the relief of the signs and symptoms of juvenile arthritis

Naproxen as naproxen suspension is recommended for juvenile rheumatoid arthritis in order to obtain the maximum dosage flexibility based on the patient’s weight.

Naproxen as naproxen tablets and naproxen sodium tablets are also indicated:

- For relief of the signs and symptoms of tendonitis
- For relief of the signs and symptoms of bursitis
- For relief of the signs and symptoms of acute gout
- For the management of pain
- For the management of primary dysmenorrhea

CONTRAINDICATIONS

Naproxen and naproxen sodium are contraindicated in patients with known hypersensitivity to naproxen and naproxen sodium.

Naproxen and naproxen sodium should not be given to patients who have experienced asthma, urticaria, or allergic-type reactions after taking aspirin or other NSAIDs. Severe, rarely fatal, anaphylactic-like reactions to NSAIDs have been reported in such patients (see WARNINGS: Anaphylactoid Reactions and PRECAUTIONS: Preexisting Asthma).

Naproxen and naproxen sodium are contraindicated for the treatment of peri-operative pain in the setting of coronary artery bypass graft (CABG) surgery (see WARNINGS).

WARNINGS

Cardiovascular Effects
Cardiovascular Thrombotic Events

Clinical trials of several COX-2 selective and nonselective NSAIDs of up to three years duration have shown an increased risk of serious cardiovascular (CV) thrombotic events, myocardial infarction, and stroke, which can be fatal. All NSAIDS, both COX-2 selective and nonselective, may have a similar risk. Patients with known CV disease or risk factors for CV disease may be at greater risk. To minimize the potential risk for an adverse CV event in patients treated with an NSAID, the lowest effective dose should be used for the shortest duration possible. Physicians and patients should remain alert for the development of such events, even in the absence of previous CV symptoms. Patients should be informed about the signs and/or symptoms of serious CV events and the steps to take if they occur.

There is no consistent evidence that concurrent use of aspirin mitigates the increased risk of serious CV thrombotic events associated with NSAID use. The concurrent use of aspirin and an NSAID does increase the risk of serious GI events (see WARNINGS: Gastrointestinal Effects - Risk of Ulceration, Bleeding, and Perforation).

Two large, controlled, clinical trials of a COX-2 selective NSAID for the treatment of pain in the first 10-14 days following CABG surgery found an increased incidence of myocardial infarction and stroke (see CONTRAINDICATIONS).

Hypertension

NSAIDs, including naproxen and naproxen sodium, can lead to onset of new hypertension or worsening of pre-existing hypertension, either of which may contribute to the increased incidence of CV events. Patients taking thiazides or loop diuretics may have impaired response to these therapies when taking NSAIDs. NSAIDs, including naproxen and naproxen sodium, should be used with caution in patients with hypertension. Blood pressure (BP) should be monitored closely during the initiation of NSAID treatment and throughout the course of therapy.

Congestive Heart Failure and Edema

Fluid retention, edema, and peripheral edema have been observed in some patients taking NSAIDs. Naproxen and naproxen sodium should be used with caution in patients with fluid retention, hypertension, or heart failure. Since each naproxen sodium tablet contains 25 mg or 50 mg of sodium (about 1 mEq per each 250 mg of naproxen), this could be considered in patients whose overall intake of sodium must be severely restricted.

Gastrointestinal Effects - Risk of Ulceration, Bleeding, and Perforation

NSAIDs, including naproxen and naproxen sodium, can cause serious gastrointestinal (GI) adverse events including inflammation, bleeding, ulceration, and perforation of the stomach, small intestine, or large intestine, which can be fatal.

These serious adverse events can occur at any time, with or without warning symptoms, in patients treated with NSAIDs. Only one in five patients, who develop a serious upper GI adverse event on NSAID therapy, is symptomatic. Upper GI ulcers, gross bleeding, or perforation caused by NSAIDs occur in approximately 1% of patients treated for 3-6 months, and in about 2-4% of patients treated for one year. These trends continue with longer duration of use, increasing the likelihood of developing a serious GI event at some time during the course of therapy. However, even short-term therapy is not without risk. The utility of periodic laboratory monitoring has not been demonstrated, nor has it been adequately assessed. Only 1 in 5 patients who develop a serious upper GI adverse event on NSAID therapy is symptomatic.

NSAIDs should be prescribed with extreme caution in those with a prior history of ulcer disease or gastrointestinal bleeding. Patients with a prior history of peptic ulcer disease and/or gastrointestinal bleeding who use NSAIDs have a greater than 10-fold increased risk for developing a GI bleed compared to patients with neither of these risk factors. Other factors that increase the risk for GI bleeding in patients treated with NSAIDs include concomitant use of oral corticosteroids or anticoagulants, longer duration of NSAID therapy, smoking, use of alcohol, older age, and poor general health status. Most spontaneous reports of fatal GI events are in elderly or debilitated patients and therefore, special care should be taken in treating this population. To minimize the potential risk for an adverse GI event in patients treated with an NSAID, the lowest effective dose should be used for the shortest possible duration. Patients and physicians should remain alert for signs and symptoms of GI ulceration and bleeding during NSAID therapy and promptly initiate additional evaluation and treatment if a serious GI adverse event is suspected. This should include discontinuation of the NSAID until a serious GI adverse event is ruled out. For high risk patients, alternate therapies that do not involve NSAIDs should be considered.

Epidemiological studies, both of the case-control and cohort design, have demonstrated as association between use of psychotropic drugs that interfere with serotonin reuptake and the occurrence of upper gastrointestinal bleeding. In two studies, concurrent use of an NSAID or aspirin potentiated the risk of bleeding (see PRECAUTIONS - Drug Interactions). Although these studies focused on upper gastrointestinal bleeding, there is reason to believe that bleeding at other sites may be similarly potentiated.

NSAIDs should be given with care to patients with a history of inflammatory bowel disease (ulcerative colitis, Crohn’s disease) as their condition may be exacerbated.

Renal Effects

Long-term administration of NSAIDs has resulted in renal papillary necrosis and other renal injury. Renal toxicity has also been seen in patients in whom renal prostaglandins have a compensatory role in the maintenance of renal perfusion. In these patients, administration of a nonsteroidal anti-inflammatory drug may cause a dose-dependent reduction in prostaglandin formation and, secondarily, in renal blood flow, which may precipitate overt renal decompensation. Patients at greatest risk of this reaction are those with impaired renal function, hypovolemia, heart failure, liver dysfunction, salt depletion, those taking diuretics and angiotensin converting enzyme (ACE) inhibitors or angiotensin receptor blockers (ARBs), and the elderly. Discontinuation of nonsteroidal anti-inflammatory drug therapy is usually followed by recovery to the pretreatment state (see WARNINGS: Advanced Renal Disease).

Advanced Renal Disease

No information is available from controlled clinical studies regarding the use of naproxen or naproxen sodium in patients with advanced renal disease. Therefore, treatment with naproxen and naproxen sodium is not recommended in these patients with advanced renal disease. If naproxen or naproxen sodium therapy must be initiated, close monitoring of the patient's renal function is advisable and patients should be adequately hydrated.

Anaphylactoid Reactions

As with other NSAIDs, anaphylactoid reactions may occur in patients without known prior exposure to naproxen or naproxen sodium. Naproxen and naproxen sodium should not be given to patients with the aspirin triad. This symptom complex typically occurs in asthmatic patients who experience rhinitis with or without nasal polyps, or who exhibit severe, potentially fatal bronchospasm after taking aspirin or other NSAIDs (see CONTRAINDICATIONS and PRECAUTIONS: Preexisting Asthma). Emergency help should be sought in cases where an anaphylactoid reaction occurs. Anaphylactoid reactions, like anaphylaxis, may have a fatal outcome.

Skin Reactions

NSAIDs, including naproxen and naproxen sodium, can cause serious skin adverse events such as exfoliative dermatitis, Stevens-Johnson Syndrome (SJS), and toxic epidermal necrolysis (TEN), which can be fatal. These serious events may occur without warning. Patients should be informed about the signs and symptoms of serious skin manifestations and use of the drug should be discontinued at the first appearance of skin rash or any other sign of hypersensitivity.

Pregnancy

In late pregnancy, as with other NSAIDs, naproxen and naproxen sodium should be avoided because it may cause premature closure of the ductus arteriosus.

PRECAUTIONS

General

Naproxen-containing products such as naproxen tablets, naproxen sodium tablets, ALEVE®, and other naproxen products should not be used concomitantly since they all circulate in the plasma as the naproxen anion.

Naproxen and naproxen sodium cannot be expected to substitute for corticosteroids or to treat corticosteroid insufficiency. Abrupt discontinuation of corticosteroids may lead to disease exacerbation. Patients on prolonged corticosteroid therapy should have their therapy tapered slowly if a decision is made to discontinue corticosteroids and the patient should be observed closely for any evidence of adverse effects, including adrenal insufficiency and exacerbation of symptoms of arthritis.

Patients with initial hemoglobin values of 10 g or less who are to receive long-term therapy should have hemoglobin values determined periodically.

The pharmacological activity of naproxen and naproxen sodium in reducing fever and inflammation may diminish the utility of these diagnostic signs in detecting complications of presumed noninfectious, noninflammatory painful conditions.

Because of adverse eye findings in animal studies with drugs of this class, it is recommended that ophthalmic studies be carried out if any change or disturbance in vision occurs.

Hepatic Effects

Borderline elevations of one or more liver tests may occur in up to 15% of patients taking NSAIDs including naproxen and naproxen sodium. Hepatic abnormalities may be the result of hypersensitivity rather than direct toxicity. These laboratory abnormalities may progress, may remain essentially unchanged, or may be transient with continued therapy. The SGPT (ALT) test is probably the most sensitive indicator of liver dysfunction. Notable elevations of ALT or AST (approximately three or more times the upper limit of normal) have been reported in approximately 1% of patients in clinical trials with NSAIDs. In addition, rare cases of severe hepatic reactions, including jaundice and fatal fulminant hepatitis, liver necrosis and hepatic failure, some of them with fatal outcomes have been reported.

A patient with symptoms and/or signs suggesting liver dysfunction, or in whom an abnormal liver test has occurred, should be evaluated for evidence of the development of more severe hepatic reaction while on therapy with naproxen or naproxen sodium.

If clinical signs and symptoms consistent with liver disease develop, or if systemic manifestations occur (eg, eosinophilia, rash, etc.), naproxen or naproxen sodium should be discontinued.

Chronic alcoholic liver disease and probably other diseases with decreased or abnormal plasma proteins (albumin) reduce the total plasma concentration of naproxen, but the plasma concentration of unbound naproxen is increased. Caution is advised when high doses are required and some adjustment of dosage may be required in these patients. It is prudent to use the lowest effective dose.

Hematological Effects

Anemia is sometimes seen in patients receiving NSAIDs, including naproxen and naproxen sodium. This may be due to fluid retention, occult or gross GI blood loss, or an incompletely described effect upon erythropoiesis. Patients on long-term treatment with NSAIDs, including naproxen and naproxen sodium, should have their hemoglobin or hematocrit checked if they exhibit any signs or symptoms of anemia.

NSAIDs inhibit platelet aggregation and have been shown to prolong bleeding time in some patients. Unlike aspirin, their effect on platelet function is quantitatively less, of shorter duration, and reversible. Patients receiving either naproxen or naproxen sodium who may be adversely affected by alterations in platelet function, such as those with coagulation disorders or patients receiving anticoagulants, should be carefully monitored.

Preexisting Asthma

Patients with asthma may have aspirin-sensitive asthma. The use of aspirin in patients with aspirin-sensitive asthma has been associated with severe bronchospasm, which can be fatal. Since cross reactivity, including bronchospasm, between aspirin and other nonsteroidal anti-inflammatory drugs has been reported in such aspirin-sensitive patients, naproxen and naproxen sodium should not be administered to patients with this form of aspirin sensitivity and should be used with caution in patients with preexisting asthma.

Information for Patients

Patients should be informed of the following information before initiating therapy with an NSAID and periodically during the course of ongoing therapy. Patients should also be encouraged to read the NSAID Medication Guide that accompanies each prescription dispensed.

- Naproxen and naproxen sodium, like other NSAIDs, may cause serious CV side effects, such as MI or stroke, which may result in hospitalization and even death. Although serious CV events can occur without warning symptoms, patients should be alert for the signs and symptoms of chest pain, shortness of breath, weakness, slurring of speech, and should ask for medical advice when observing any indicative sign or symptoms. Patients should be apprised of the importance of this follow-up (see WARNINGS: Cardiovascular Effects).
- Naproxen and naproxen sodium, like other NSAIDs, can cause GI discomfort and, rarely, serious GI side effects, such as ulcers and bleeding, which may result in hospitalization and even death. Although serious GI tract ulcerations and bleeding can occur without warning symptoms, patients should be alert for the signs and symptoms of ulcerations and bleeding, and should ask for medical advice when observing any indicative sign or symptoms including epigastric pain, dyspepsia, melena, and hematemesis. Patients should be apprised of the importance of this follow-up (see WARNINGS: Gastrointestinal Effects - Risk of Ulceration, Bleeding, and Perforation)
- Naproxen and naproxen sodium, like other NSAIDs, can cause serious skin side effects such as exfoliative dermatitis, SJS, and TEN, which may result in hospitalizations and even death. Although serious skin reactions may occur without warning, patients should be alert for the signs and symptoms of skin rash and blisters, fever, or other signs of hypersensitivity such as itching, and should ask for medical advice when observing any indicative signs or symptoms. Patients should be advised to stop the drug immediately if they develop any type of rash and contact their physicians as soon as possible.
- Patients should promptly report signs or symptoms of unexplained weight gain or edema to their physicians.
- Patients should be informed of the warning signs and symptoms of hepatotoxicity (eg, nausea, fatigue, lethargy, pruritus, jaundice, right upper quadrant tenderness, and “flu-like” symptoms). If these occur, patients should be instructed to stop therapy and seek immediate medical therapy.
- Patients should be informed of the signs of an anaphylactoid reaction (eg, difficulty breathing, swelling of the face or throat). If these occur, patients should be instructed to seek immediate emergency help (see WARNINGS).
- In late pregnancy, as with other NSAIDs, naproxen and naproxen sodium should be avoided because it may cause premature closure of the ductus arteriosus.
- Caution should be exercised by patients whose activities require alertness if they experience drowsiness, dizziness, vertigo or depression during therapy with naproxen.

Laboratory Tests

Because serious GI tract ulcerations and bleeding can occur without warning symptoms, physicians should monitor for signs or symptoms of GI bleeding. Patients on long-term treatment with NSAIDs should have their CBC and a chemistry profile checked periodically. If clinical signs and symptoms consistent with liver or renal disease develop, systemic manifestations occur (eg, eosinophilia, rash, etc.) or if abnormal liver tests persist or worsen, naproxen and naproxen sodium should be discontinued.

Drug Interactions

Angiotensin Converting Enzyme (ACE)-inhibitors/Angiotensin Receptor Blockers (ARBs)

NSAIDs may diminish the antihypertensive effect of ACE-inhibitors, ARBs, or beta-blockers (including propanolol).

Monitor patients taking NSAIDs concomitantly with ACE-inhibitors, ARBs, or beta blockers for changes in blood pressure.

In addition, in patients who are elderly, volume-depleted (including those on diuretic therapy), or have compromised renal function, co-administration of NSAIDs with ACE inhibitors or ARBs may result in deterioration of renal function, including possible acute renal failure. Monitor these patients closely for signs of worsening renal function

Antacids and Sucralfate

Concomitant administration of some antacids (magnesium oxide or aluminum hydroxide) and sucralfate can delay the absorption of naproxen.

Aspirin

When naproxen as naproxen tablets or naproxen sodium tablets is administered with aspirin, its protein binding is reduced, although the clearance of free naproxen or naproxen sodium is not altered. The clinical significance of this interaction is not known; however, as with other NSAIDs, concomitant administration of naproxen and naproxen sodium and aspirin is not generally recommended because of the potential of increased adverse effects.

Cholestyramine

As with other NSAIDs, concomitant administration of cholestyramine can delay the absorption of naproxen.

Diuretics

Clinical studies, as well as postmarketing observations, have shown that naproxen and naproxen sodium can reduce the natriuretic effect of furosemide and thiazides in some patients. This response has been attributed to inhibition of renal prostaglandin synthesis. During concomitant therapy with NSAIDs, the patient should be observed closely for signs of renal failure (see WARNINGS: Renal Effects), as well as to assure diuretic efficacy.

Lithium

NSAIDs have produced an elevation of plasma lithium levels and a reduction in renal lithium clearance. The mean minimum lithium concentration increased 15% and the renal clearance was decreased by approximately 20%. These effects have been attributed to inhibition of renal prostaglandin synthesis by the NSAID. Thus, when NSAIDs and lithium are administered concurrently, subjects should be observed carefully for signs of lithium toxicity.

Methotrexate

NSAIDs have been reported to competitively inhibit methotrexate accumulation in rabbit kidney slices. Naproxen, naproxen sodium and other nonsteroidal anti-inflammatory drugs have been reported to reduce the tubular secretion of methotrexate in an animal model. This may indicate that they could enhance the toxicity of methotrexate. Caution should be used when NSAIDs are administered concomitantly with methotrexate.

Warfarin

The effects of warfarin and NSAIDs on GI bleeding are synergistic, such that users of both drugs together have a risk of serious GI bleeding higher than users of either drug alone. No significant interactions have been observed in clinical studies with naproxen and coumarin-type anticoagulants. However, caution is advised since interactions have been seen with other nonsteroidal agents of this class. The free fraction of warfarin may increase substantially in some subjects and naproxen interferes with platelet function.

Selective Serotonin Reuptake Inhibitors (SSRIs)

There is an increased risk of gastrointestinal bleeding when selective serotonin reuptake inhibitors (SSRIs) are combined with NSAIDs. Caution should be used when NSAIDs are administered concomitantly with SSRIs.

Other Information Concerning Drug Interactions

Naproxen is highly bound to plasma albumin; it thus has a theoretical potential for interaction with other albumin-bound drugs such as coumarin-type anticoagulants, sulphonylureas, hydantoins, other NSAIDs, and aspirin. Patients simultaneously receiving naproxen and a hydantoin, sulphonamide or sulphonylurea should be observed for adjustment of dose if required.

Probenecid given concurrently increases naproxen anion plasma levels and extends its plasma half-life significantly.

Drug/Laboratory Test Interaction

Naproxen may decrease platelet aggregation and prolong bleeding time. This effect should be kept in mind when bleeding times are determined.

The administration of naproxen may result in increased urinary values for 17-ketogenic steroids because of an interaction between the drug and/or its metabolites with m-di-nitrobenzene used in this assay. Although 17-hydroxycorticosteroid measurements (Porter-Silber test) do not appear to be artifactually altered, it is suggested that therapy with naproxen be temporarily discontinued 72 hours before adrenal function tests are performed if the Porter-Silber test is to be used.

Naproxen may interfere with some urinary assays of 5-hydroxy indoleacetic acid (5HIAA).

Carcinogenesis

A 2-year study was performed in rats to evaluate the carcinogenic potential of naproxen at rat doses of 8, 16, and 24 mg/kg/day (50, 100, and 150 mg/m^2). The maximum dose used was 0.28 times the systemic exposure to humans at the recommended dose. No evidence of tumorigenicity was found.

Pregnancy

Teratogenic Effects

Pregnancy Category C

Reproduction studies have been performed in rats at 20 mg/kg/day (125 mg/m^2/day, 0.23 times the human systemic exposure), rabbits at 20 mg/kg/day (220 mg/m^2/day, 0.27 times the human systemic exposure), and mice at 170 mg/kg/day (510 mg/m^2/day, 0.28 times the human systemic exposure) with no evidence of impaired fertility or harm to the fetus due to the drug. However, animal reproduction studies are not always predictive of human response. There are no adequate and well-controlled studies in pregnant women. Naproxen and naproxen sodium should be used in pregnancy only if the potential benefit justifies the potential risk to the fetus.

Nonteratogenic Effects

There is some evidence to suggest that when inhibitors of prostaglandin synthesis are used to delay preterm labor there is an increased risk of neonatal complications such as necrotizing enterocolitis, patent ductus arteriosus and intracranial hemorrhage. Naproxen treatment given in late pregnancy to delay parturition has been associated with persistent pulmonary hypertension, renal dysfunction and abnormal prostaglandin E levels in preterm infants. Because of the known effects of nonsteroidal anti-inflammatory drugs on the fetal cardiovascular system (closure of ductus arteriosus), use during pregnancy (particularly late pregnancy) should be avoided.

Labor and Delivery

In rat studies with NSAIDs, as with other drugs known to inhibit prostaglandin synthesis, an increased incidence of dystocia, delayed parturition, and decreased pup survival occurred. Naproxen-containing products are not recommended in labor and delivery because, through its prostaglandin synthesis inhibitory effect, naproxen may adversely affect fetal circulation and inhibit uterine contractions, thus increasing the risk of uterine hemorrhage. The effects of naproxen and naproxen sodium on labor and delivery in pregnant women are unknown.

Nursing Mothers

The naproxen anion has been found in the milk of lactating women at a concentration equivalent to approximately 1% of maximum naproxen concentration in plasma. Because of the possible adverse effects of prostaglandin-inhibiting drugs on neonates, use in nursing mothers should be avoided.

Pediatric Use

Safety and effectiveness in pediatric patients below the age of 2 years have not been established. Pediatric dosing recommendations for juvenile arthritis are based on well-controlled studies (see DOSAGE AND ADMINISTRATION). There are no adequate effectiveness or dose-response data for other pediatric conditions, but the experience in juvenile arthritis and other use experience have established that single doses of 2.5 to 5 mg/kg (as naproxen suspension, see DOSAGE AND ADMINISTRATION), with total daily dose not exceeding 15 mg/kg/day, are well tolerated in pediatric patients over 2 years of age.

Geriatric Use

Studies indicate that although total plasma concentration of naproxen is unchanged, the unbound plasma fraction of naproxen is increased in the elderly. Caution is advised when high doses are required and some adjustment of dosage may be required in elderly patients. As with other drugs used in the elderly, it is prudent to use the lowest effective dose.

Experience indicates that geriatric patients may be particularly sensitive to certain adverse effects of nonsteroidal anti-inflammatory drugs. Elderly or debilitated patients seem to tolerate peptic ulceration or bleeding less well when these events do occur. Most spontaneous reports of fatal GI events are in the geriatric population (see WARNINGS).

Naproxen is known to be substantially excreted by the kidney, and the risk of toxic reactions to this drug may be greater in patients with impaired renal function. Because elderly patients are more likely to have decreased renal function, care should be taken in dose selection, and it may be useful to monitor renal function. Geriatric patients may be at a greater risk for the development of a form of renal toxicity precipitated by reduced prostaglandin formation during administration of nonsteroidal anti-inflammatory drugs (see WARNINGS: Renal Effects).

ADVERSE REACTIONS

Adverse reactions reported in controlled clinical trials in 960 patients treated for rheumatoid arthritis or osteoarthritis are listed below. In general, reactions in patients treated chronically were reported 2 to 10 times more frequently than they were in short-term studies in the 962 patients treated for mild to moderate pain or for dysmenorrhea. The most frequent complaints reported related to the gastrointestinal tract.

A clinical study found gastrointestinal reactions to be more frequent and more severe in rheumatoid arthritis patients taking daily doses of 1500 mg naproxen compared to those taking 750 mg naproxen (see CLINICAL PHARMACOLOGY).

In controlled clinical trials with about 80 pediatric patients and in well-monitored, open-label studies with about 400 pediatric patients with juvenile arthritis treated with naproxen, the incidence of rash and prolonged bleeding times were increased, the incidence of gastrointestinal and central nervous system reactions were about the same, and the incidence of other reactions were lower in pediatric patients than in adults.

In patients taking naproxen in clinical trials, the most frequently reported adverse experiences in approximately 1% to 10% of patients are:

Gastrointestinal (GI) Experiences, including: heartburn*, abdominal pain*, nausea*, constipation*, diarrhea, dyspepsia, stomatitis

Central Nervous System: headache*, dizziness*, drowsiness*, lightheadedness, vertigo

Dermatologic: pruritus (itching)*, skin eruptions*, ecchymoses*, sweating, purpura

Special Senses: tinnitus*, visual disturbances, hearing disturbances

Cardiovascular: edema*, palpitations

General: dyspnea*, thirst

*Incidence of reported reaction between 3% and 9%. Those reactions occurring in less than 3% of the patients are unmarked.

In patients taking NSAIDs, the following adverse experiences have also been reported in approximately 1% to 10% of patients.

Gastrointestinal (GI) Experiences, including: flatulence, gross bleeding/perforation, GI ulcers (gastric/duodenal), vomiting

General: abnormal renal function, anemia, elevated liver enzymes, increased bleeding time, rashes

The following are additional adverse experiences reported in <1% of patients taking naproxen during clinical trials and through postmarketing reports. Those adverse reactions observed through postmarketing reports are italicized.

Body as a Whole: anaphylactoid reactions, angioneurotic edema, menstrual disorders, pyrexia (chills and fever)

Cardiovascular: congestive heart failure, vasculitis, hypertension, pulmonary edema

Gastrointestinal: inflammation, bleeding (sometimes fatal, particularly in the elderly), ulceration, perforation and obstruction of the upper or lower gastrointestinal tract. Esophagitis, stomatitis, hematemesis, pancreatitis, vomiting, colitis, exacerbation of inflammatory bowel disease (ulcerative colitis, Crohn’s disease)

Hepatobiliary: jaundice, abnormal liver function tests, hepatitis (some cases have been fatal)

Hemic and Lymphatic: eosinophilia, leucopenia, melena, thrombocytopenia, agranulocytosis, granulocytopenia, hemolytic anemia, aplastic anemia

Metabolic and Nutritional: hyperglycemia, hypoglycemia

Nervous System: inability to concentrate, depression, dream abnormalities, insomnia, malaise, myalgia, muscle weakness, aseptic meningitis, cognitive dysfunction, convulsions

Respiratory: eosinophilic pneumonitis, asthma

Dermatologic: alopecia, urticaria, skin rashes, toxic epidermal necrolysis, erythema multiforme, erythema nodosum, fixed drug eruption, lichen planus, pustular reaction, systemic lupus erythematoses, bullous reactions, including Stevens-Johnson syndrome, photosensitive dermatitis, photosensitivity reactions, including rare cases resembling porphyria cutanea tarda (pseudoporphyria) or epidermolysis bullosa. If skin fragility, blistering or other symptoms suggestive of pseudoporphyria occur, treatment should be discontinued and the patient monitored.

Special Senses: hearing impairment, corneal opacity, papillitis, retrobulbar optic neuritis, papilledema

Urogenital: glomerular nephritis, hematuria, hyperkalemia, interstitial nephritis, nephrotic syndrome, renal disease, renal failure, renal papillary necrosis, raised serum creatinine

Reproduction (female): infertility

In patients taking NSAIDs, the following adverse experiences have also been reported in <1% of patients.

Body as a Whole: fever, infection, sepsis, anaphylactic reactions, appetite changes, death

Cardiovascular: hypertension, tachycardia, syncope, arrhythmia, hypotension, myocardial infarction

Gastrointestinal: dry mouth, esophagitis, gastric/peptic ulcers, gastritis, glossitis, eructation

Hepatobiliary: hepatitis, liver failure

Hemic and Lymphatic: rectal bleeding, lymphadenopathy, pancytopenia

Metabolic and Nutritional: weight changes

Nervous System: anxiety, asthenia, confusion, nervousness, paresthesia, somnolence, tremors, convulsions, coma, hallucinations

Respiratory: asthma, respiratory depression, pneumonia

Dermatologic: exfoliative dermatitis

Special Senses: blurred vision, conjunctivitis

Urogenital: cystitis, dysuria, oliguria/polyuria, proteinuria

OVERDOSAGE

Symptoms and Signs

Significant naproxen overdosage may be characterized by lethargy, dizziness, drowsiness, epigastric pain, abdominal discomfort, heartburn, indigestion, nausea, transient alterations in liver function, hypoprothrombinemia, renal dysfunction, metabolic acidosis, apnea, disorientation or vomiting. Gastrointestinal bleeding can occur. Hypertension, acute renal failure, respiratory depression, and coma may occur, but are rare. Anaphylactoid reactions have been reported with therapeutic ingestion of NSAIDs, and may occur following an overdose. Because naproxen sodium may be rapidly absorbed, high and early blood levels should be anticipated. A few patients have experienced convulsions, but it is not clear whether or not these were drug-related. It is not known what dose of the drug would be life threatening. The oral LD50 of the drug is 543 mg/kg in rats, 1234 mg/kg in mice, 4110 mg/kg in hamsters, and greater than 1000 mg/kg in dogs.

Treatment

Patients should be managed by symptomatic and supportive care following a NSAID overdose. There are no specific antidotes. Hemodialysis does not decrease the plasma concentration of naproxen because of the high degree of its protein binding. Emesis and/or activated charcoal (60 to 100 g in adults, 1 to 2 g/kg in children) and/or osmotic cathartic may be indicated in patients seen within 4 hours of ingestion with symptoms or following a large overdose. Forced diuresis, alkalinization of urine or hemoperfusion may not be useful due to high protein binding.

DOSAGE AND ADMINISTRATION

Carefully consider the potential benefits and risks of naproxen, naproxen sodium and other treatment options before deciding to use naproxen tablets and naproxen sodium tablets. Use the lowest effective dose for the shortest duration consistent with individual patient treatment goals (see WARNINGS).

After observing the response to initial therapy with naproxen or naproxen sodium, the dose and frequency should be adjusted to suit an individual patient's needs.

Different dose strengths and formulations (ie, tablets, suspension) of the drug are not necessarily bioequivalent. This difference should be taken into consideration when changing formulation.

Although naproxen and naproxen sodium circulate in the plasma as naproxen, they have pharmacokinetic differences that may affect onset of action. Onset of pain relief can begin within 30 minutes in patients taking naproxen sodium and within 1 hour in patients taking naproxen.

The recommended strategy for initiating therapy is to choose a formulation and a starting dose likely to be effective for the patient and then adjust the dosage based on observation of benefit and/or adverse events. A lower dose should be considered in patients with renal or hepatic impairment or in elderly patients (see WARNINGS and PRECAUTIONS).

Geriatric Patients

Studies indicate that although total plasma concentration of naproxen is unchanged, the unbound plasma fraction of naproxen is increased in the elderly. Caution is advised when high doses are required and some adjustment of dosage may be required in elderly patients. As with other drugs used in the elderly, it is prudent to use the lowest effective dose.

Patients With Moderate to Severe Renal Impairment

Naproxen-containing products are not recommended for use in patients with moderate to severe and severe renal impairment (creatinine clearance <30 mL/min) (see WARNINGS: Renal Effects).

Rheumatoid Arthritis, Osteoarthritis and Ankylosing Spondylitis
Naproxen | 250 mg; or 375 mg; or 500 mg | twice daily; twice daily; twice daily
Naproxen sodium | 275 mg (naproxen 250 mg with 25 mg sodium); 550 mg (naproxen 500 mg with 50 mg sodium) | twice daily; twice daily

During long-term administration, the dose of naproxen may be adjusted up or down depending on the clinical response of the patient. A lower daily dose may suffice for long-term administration. The morning and evening doses do not have to be equal in size and the administration of the drug more frequently than twice daily is not necessary.

In patients who tolerate lower doses well, the dose may be increased to naproxen 1500 mg/day for limited periods of up to 6 months when a higher level of anti-inflammatory/analgesic activity is required. When treating such patients with naproxen 1500 mg/day, the physician should observe sufficient increased clinical benefits to offset the potential increased risk. The morning and evening doses do not have to be equal in size and administration of the drug more frequently than twice daily does not generally make a difference in response (see CLINICAL PHARMACOLOGY).

Juvenile Arthritis

The recommended total daily dose of naproxen is approximately 10 mg/kg given in 2 divided doses (ie, 5 mg/kg given twice a day).

Management of Pain, Primary Dysmenorrhea, and Acute Tendonitis and Bursitis

The recommended starting dose is 550 mg of naproxen sodium as naproxen sodium tablet followed by 550 mg every 12 hours or 275 mg every 6 to 8 hours as required. The initial total daily dose should not exceed 1375 mg of naproxen sodium. Thereafter, the total daily dose should not exceed 1100 mg of naproxen sodium. Because the sodium salt of naproxen is more rapidly absorbed, naproxen sodium tablets are recommended for the management of acute painful conditions when prompt onset of pain relief is desired. Naproxen may also be used for initial treatment of acute pain because absorption of naproxen is delayed compared to other naproxen-containing products (see CLINICAL PHARMACOLOGY, INDICATIONS AND USAGE).

Acute Gout

The recommended starting dose is 750 mg of naproxen followed by 250 mg every 8 hours until the attack has subsided. Naproxen sodium may also be used at a starting dose of 825 mg followed by 275 mg every 8 hours.

HOW SUPPLIED

Naproxen Tablets USP:

250 mg: circular, light orange colored, flat, uncoated tablets, engraved with ‘G’ and ‘32’ on either side of break line on one side and ‘250’ on the other side. Packaged in light-resistant bottles of 15, 30, 45, 60, and 90..

15’s (bottle): NDC 63187-461-15

30’s (bottle): NDC 63187-461-30

45’s (bottle): NDC 63187-461-45

60’s (bottle): NDC 63187-461-60

90’s (bottle): NDC 63187-461-90

Store at 15° to 30°C (59° to 86°F) in well-closed containers.

ALEVE® is a registered trademark of Bayer Healthcare LLC

Manufactured by:
Glenmark Generics Ltd
India

Manufactured for:

Glenmark Generics Inc., USA
Mahwah, NJ 07430

Repackaged by:

Proficient Rx LP

Thousand Oaks, CA 91320

Questions? 1 (888)721-7115

www.glenmarkgenerics.com

November 2014

Medication Guide for Non-Steroidal Anti-Inflammatory Drugs (NSAIDs)

(See the end of this Medication Guide for a list of prescription NSAID medicines.)

What is the most important information I should know about medicines called Non-Steroidal Anti-Inflammatory Drugs (NSAIDs)?

NSAID medicines may increase the chance of a heart attack or stroke that can lead to death. This chance increases:

- with longer use of NSAID medicines
- in people who have heart disease

NSAID medicines should never be used right before or after a heart surgery called a “coronary artery bypass graft (CABG).”

NSAID medicines can cause ulcers and bleeding in the stomach and intestines at any time during treatment. Ulcers and bleeding:

- can happen without warning symptoms
- may cause death

The chance of a person getting an ulcer or bleeding increases with:

- taking medicines called “corticosteroids” and “anticoagulants”
- longer use
- smoking
- drinking alcohol
- older age
- having poor health

NSAID medicines should only be used:

- exactly as prescribed
- at the lowest dose possible for your treatment
- for the shortest time needed

What are Non-Steroidal Anti-Inflammatory Drugs (NSAIDs)?

NSAID medicines are used to treat pain and redness, swelling, and heat (inflammation) from medical conditions such as:

- different types of arthritis
- menstrual cramps and other types of short-term pain

Who should not take a Non-Steroidal Anti-Inflammatory Drug (NSAID)?

Do not take an NSAID medicine:

- if you had an asthma attack, hives, or other allergic reaction with aspirin or any other NSAID medicine
- for pain right before or after heart bypass surgery

Tell your healthcare provider:

- about all your medical conditions.
- about all of the medicines you take. NSAIDs and some other medicines can interact with each other and cause serious side effects. Keep a list of your medicines to show to your healthcare provider and pharmacist.
- if you are pregnant. NSAID medicines should not be used by pregnant women late in their pregnancy.
- if you are breastfeeding. Talk to your doctor.

What are the possible side effects of Non-Steroidal Anti-Inflammatory Drugs (NSAIDs)?
Serious side effects include: | Other side effects include:
- heart attack | - stomach pain
- stroke | - constipation
- high blood pressure | - diarrhea
- heart failure from body swelling (fluid retention) | - gas
- kidney problems including kidney failure | - heartburn
- bleeding and ulcers in the stomach and intestine | - nausea
- low red blood cells (anemia) | - vomiting
- life-threatening skin reactions | - dizziness
- life-threatening allergic reactions
- liver problems including liver failure
- asthma attacks in people who have asthma

Get emergency help right away if you have any of the following symptoms:

- shortness of breath or trouble breathing
- slurred speech
- chest pain
- swelling of the face or throat
- weakness in one part or side of your body

Stop your NSAID medicine and call your healthcare provider right away if you have any of the following symptoms:

- nausea
- there is blood in your bowel movement or it is black and sticky like tar
- more tired or weaker than usual
- itching
- your skin or eyes look yellow
- unusual weight gain
- stomach pain
- skin rash or blisters with fever
- flu-like symptoms
- swelling of the arms and legs, hands and feet
- vomit blood

These are not all the side effects with NSAID medicines. Talk to your healthcare provider or pharmacist for more information about NSAID medicines. Call your doctor for medical advice about side effects. You may report side effects to FDA at 1-800-FDA-1088 or Glenmark Generics Inc., USA at 1 (888)721-7115.

Other information about Non-Steroidal Anti-Inflammatory Drugs (NSAIDs)

- Aspirin is an NSAID medicine but it does not increase the chance of a heart attack. Aspirin can cause bleeding in the brain, stomach, and intestines. Aspirin can also cause ulcers in the stomach and intestines.
- Some of these NSAID medicines are sold in lower doses without a prescription (over- the-counter). Talk to your healthcare provider before using over-the- counter NSAIDs for more than 10 days.

NSAID medicines that need a prescription
Generic Name | Tradename
Celecoxib | Celebrex®
Diclofenac | Cataflam®, Voltaren®, Arthrotec™ (combined with misoprostol)
Diflunisal | Dolobid®
Etodolac | Lodine®, Lodine® XL
Fenoprofen | Nalfon®, Nalfon® 200
Flurbirofen | Ansaid®
Ibuprofen | Motrin®, Tab-Profen®, Vicoprofen®*(combined with hydrocodone),
 | CombunoxTM (combined with oxycodone)
Indomethacin | Indocin®, Indocin® SR, Indo-Lemmon™, Indomethagan™
Ketoprofen | Oruvail®
Ketorolac | Toradol®
Mefenamic Acid | Ponstel®
Meloxicam | Mobic®
Nabumetone | Relafen®
Naproxen | Naprosyn®, Anaprox®, Anaprox® DS, EC-Naproxyn®, Naprelan®, Naprapac ® (copackaged with lansoprazole)
Oxaprozin | Daypro®
Piroxicam | Feldene®
Sulindac | Clinoril®
Tolmetin | Tolectin®, Tolectin DS®, Tolectin® 600

This Medication Guide has been approved by the U.S. Food and Drug Administration.

Trademarks are the property of their respective owners.

Manufactured by:
Glenmark Generics Ltd
India

Manufactured for:

Glenmark Generics Inc., USA
Mahwah, NJ 07430

Repackaged by:

Proficient Rx LP

Thousand Oaks, CA 91320

Questions? 1 (888)721-7115
www.glenmarkgenerics.com

November 2014